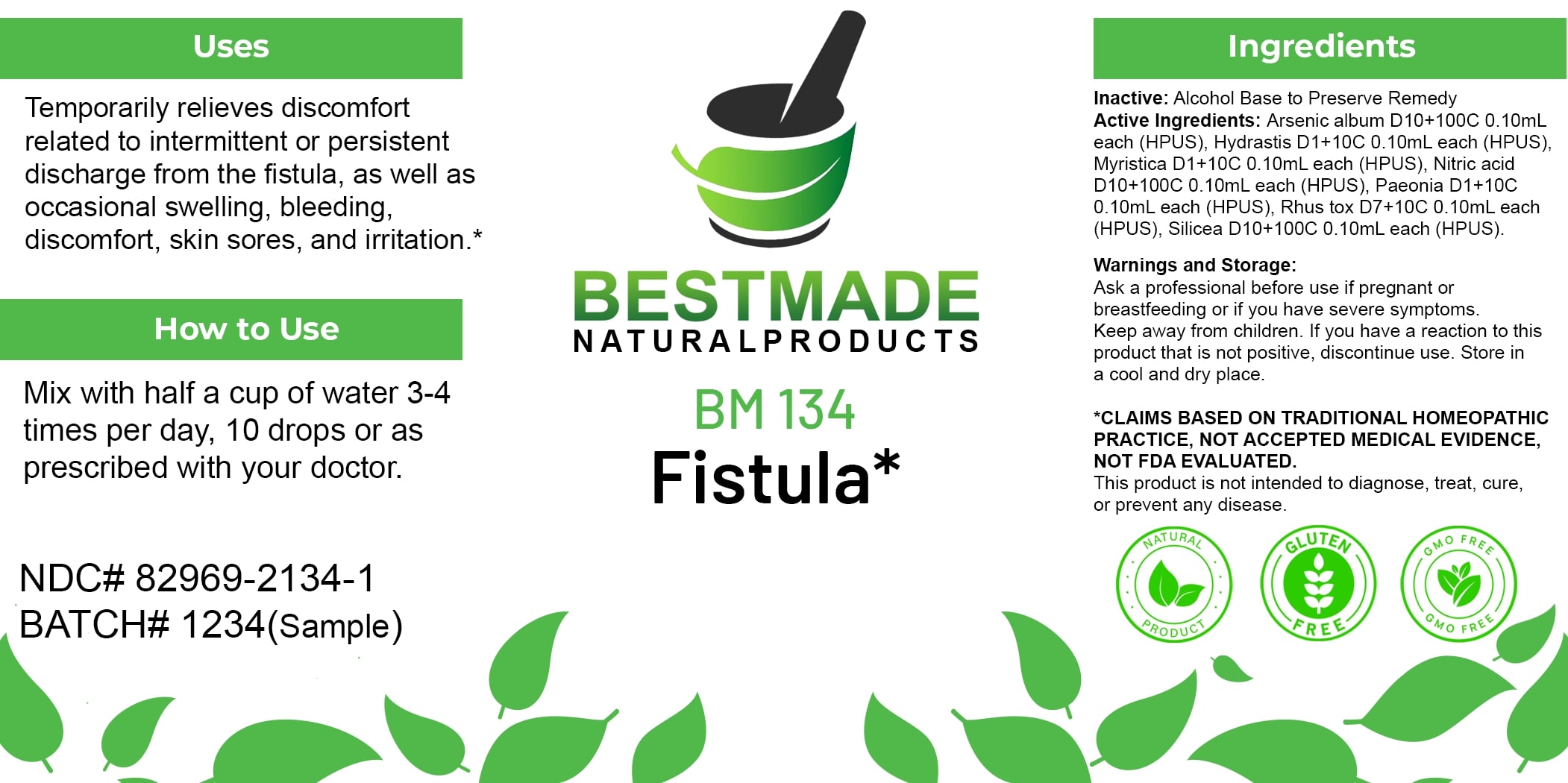 DRUG LABEL: Bestmade Natural Products BM134
NDC: 82969-2134 | Form: LIQUID
Manufacturer: Bestmade Natural Products
Category: homeopathic | Type: HUMAN OTC DRUG LABEL
Date: 20250212

ACTIVE INGREDIENTS: NITRIC ACID 30 [hp_C]/30 [hp_C]; GOLDENSEAL 30 [hp_C]/30 [hp_C]; SILICON DIOXIDE 30 [hp_C]/30 [hp_C]; VIROLA SEBIFERA RESIN 30 [hp_C]/30 [hp_C]; ARSENIC TRIOXIDE 30 [hp_C]/30 [hp_C]; TOXICODENDRON PUBESCENS LEAF 30 [hp_C]/30 [hp_C]; PAEONIA OFFICINALIS ROOT 30 [hp_C]/30 [hp_C]
INACTIVE INGREDIENTS: ALCOHOL 30 [hp_C]/30 [hp_C]

BM134

DOSAGE AND ADMINISTRATION

How to Use

Mix with half a cup of water 3-4 times per day, 10 drops or as prescribed with your doctor.

ACTIVE INGREDIENT

Active Ingredients: Arsenic album D10+100C 0.10mL each (HPUS), Hydrastis D1+10C 0.10mL each (HPUS), Myristica D1+10C 0.10mL each (HPUS), Nitric acid D10+100C 0.10mL each (HPUS), Paeonia D1+10C 0.10mL each (HPUS), Rhus tox D7+10C 0.10mL each (HPUS), Silicea D10+100C 0.10mL each (HPUS)

INACTIVE INGREDIENT

Ingredients

Inactive: Alcohol Base to Preserve Remedy

Uses

Temporarily relieves discomfort related to intermittent or persistent discharge from the fistula, as well as occasional swelling, bleeding, discomfort, skin sores, and irritation.*

*CLAIMS BASED ON TRADITIONAL HOMEOPATHIC PRACTICE, NOT ACCEPTED MEDICAL EVIDENCE, NOT FDA EVALUATED.

This product is not intended to diagnose, treat, cure, or prevent any disease.

Uses

Temporarily relieves discomfort related to intermittent or persistent discharge from the fistula, as well as occasional swelling, bleeding, discomfort, skin sores, and irritation.*

*CLAIMS BASED ON TRADITIONAL HOMEOPATHIC PRACTICE, NOT ACCEPTED MEDICAL EVIDENCE, NOT FDA EVALUATED.

This product is not intended to diagnose, treat, cure, or prevent any disease.

KEEP OUT OF REACH OF CHILDREN

Warnings and Storage:

Ask a professional before use if pregnant or breastfeeding or if you have severe symptoms. Keep away from children. If you have a reaction to this product that is not positive, discontinue use. Store in a cool and dry place.

Warnings and Storage:

Ask a professional before use if pregnant or breastfeeding or if you have severe symptoms. Keep away from children. If you have a reaction to this product that is not positive, discontinue use. Store in a cool and dry place.

*CLAIMS BASED ON TRADITIONAL HOMEOPATHIC PRACTICE, NOT ACCEPTED MEDICAL EVIDENCE, NOT FDA EVALUATED.

This product is not intended to diagnose, treat, cure, or prevent any disease.

Entire package label